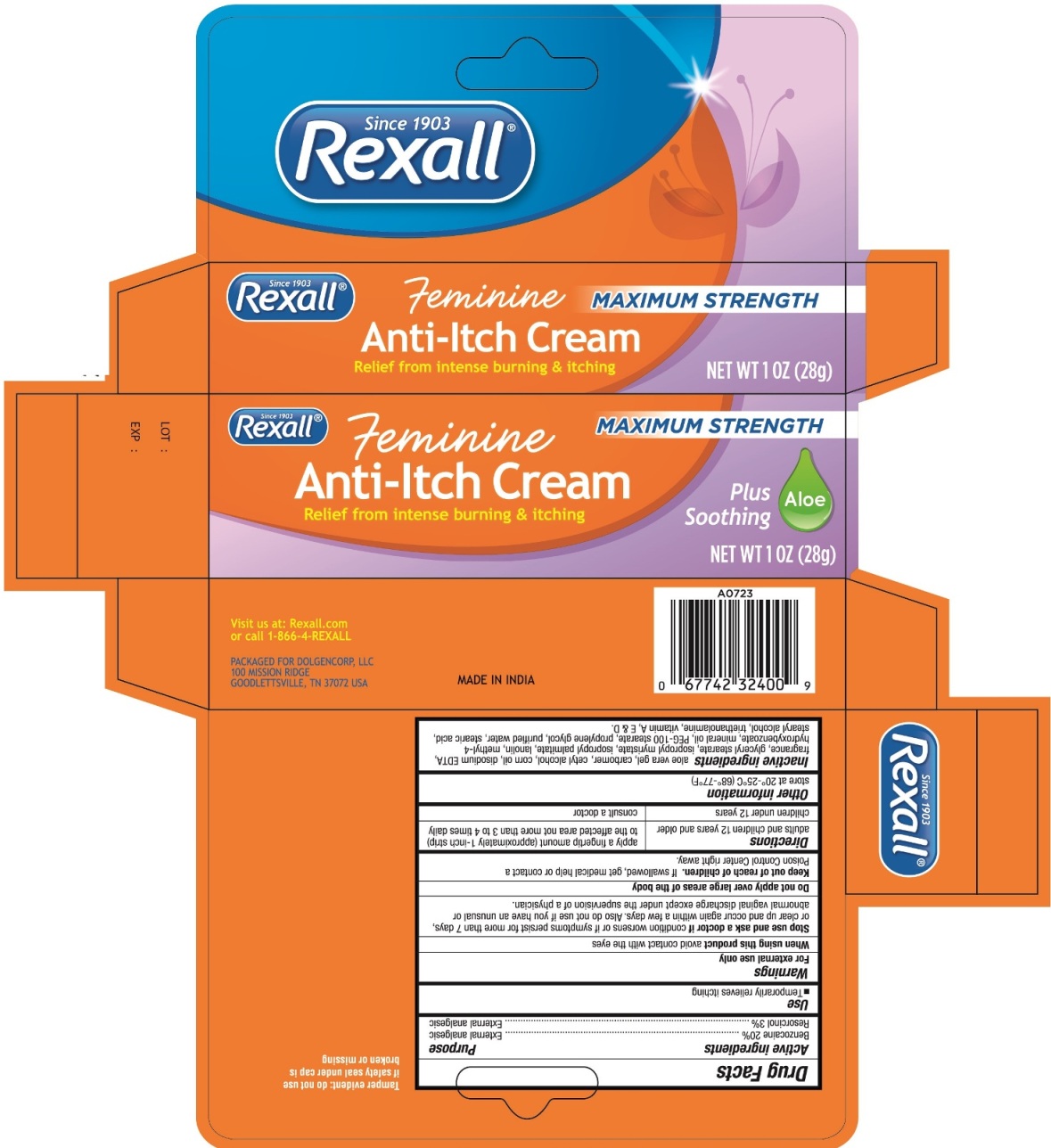 DRUG LABEL: REXALL FEMININE MAXIMUM STRENGTH ANTI-ITCH
NDC: 55910-415 | Form: CREAM
Manufacturer: Dolgencorp, Inc.
Category: otc | Type: HUMAN OTC DRUG LABEL
Date: 20160928

ACTIVE INGREDIENTS: BENZOCAINE 20 g/100 g; RESORCINOL 3 g/100 g
INACTIVE INGREDIENTS: ALOE VERA LEAF; CARBOXYPOLYMETHYLENE; CETYL ALCOHOL; CORN OIL; EDETATE DISODIUM; GLYCERYL MONOSTEARATE; ISOPROPYL MYRISTATE; ISOPROPYL PALMITATE; LANOLIN; METHYLPARABEN; MINERAL OIL; PEG-100 STEARATE; PROPYLENE GLYCOL; WATER; STEARIC ACID; STEARYL ALCOHOL; TROLAMINE; VITAMIN A; VITAMIN D; .ALPHA.-TOCOPHEROL

REXALL FEMININE MAXIMUM STRENGTH ANTI-ITCH CREAM

Active ingredients

Benzocaine 20%

Resorcinol 3%

Purpose

External Analgesic

External Analgesic

Use

- Temporarily relieves itching

Warnings

For external use only

When using this product avoid contact with eyes

Stop use and ask a doctor if condition worsens, or if symptoms persist for more than 7 days or clear up and occur again within a few days. Also, do not use if you have an unusual or abnormal vaginal discharge except under the supervision of a physician.

Do not apply over large areas of the body.

Keep out of reach of children. If swallowed, get medical help or contact a Poison Control Center right away.

Directions

adults and children 12 years and older

apply a fingertip amount (approximately 1-inch strip) to Tthe affected area not more than 3 to 4 times daily

children under 12 years

consult a doctor

Other information

store at 20°-25°C (68°-77°F)

Inactive ingredients

aloe vera gel, carbomer, cetyl alcohol, corn oil, disodium EDTA, fragrance, glyceryl stearate, isopropyl myristate, isopropyl palmitate, lanolin, methyl-4 hydroxybenzoate, mineral oil, PEG-100 stearate, propylene glycol, purified water, stearic acid, stearyl alcohol, triethanolamine, vitamin A, E & D

Principal display panel - 28 g Carton Label

REXALL FEMININE MAXIMUM STRENGTH ANTI-ITCH CREAM

NET WT 1 OZ (28 g)